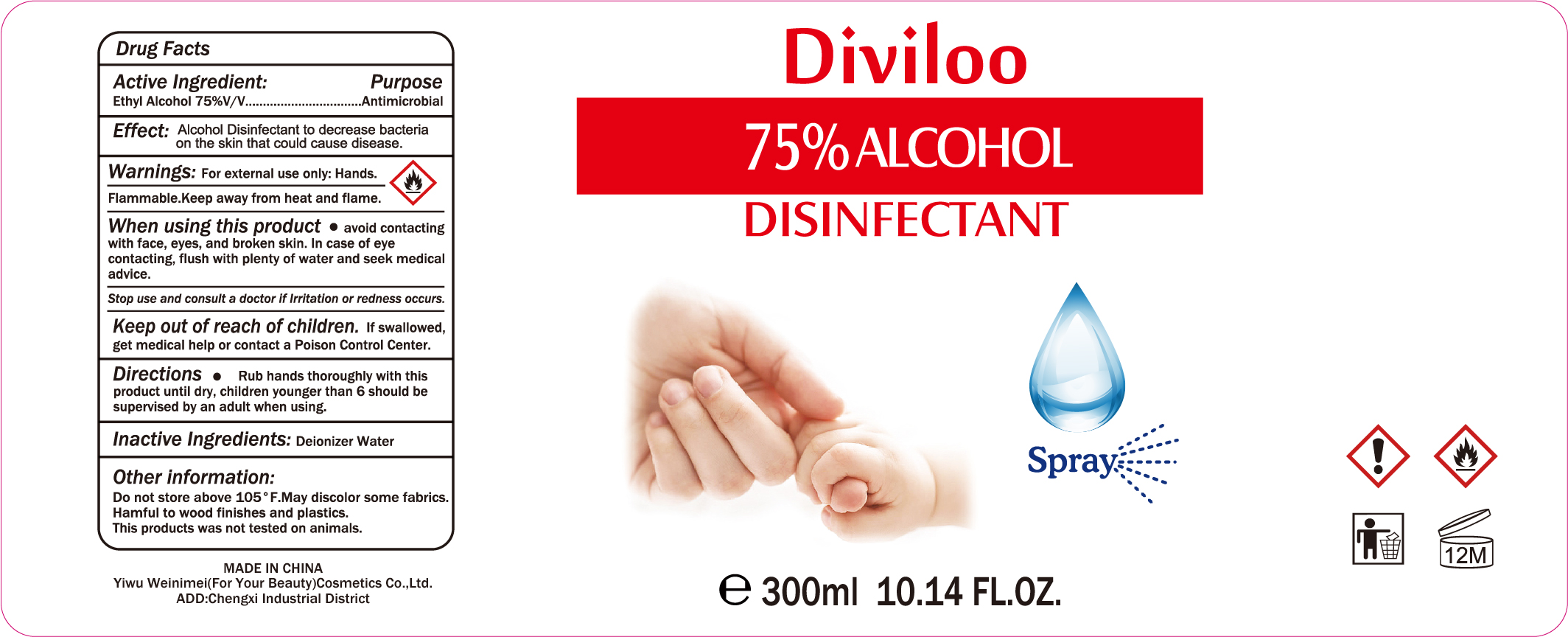 DRUG LABEL: Diviloo 75 Percent Alcohol Disinfectant
NDC: 77937-002 | Form: SPRAY
Manufacturer: Yiwu Weinimei (For Your Beauty) Cosmetics Co.,Ltd.
Category: otc | Type: HUMAN OTC DRUG LABEL
Date: 20200516

ACTIVE INGREDIENTS: ALCOHOL 75 mL/100 mL
INACTIVE INGREDIENTS: WATER

NA

Active Ingredient(s)

Ethyl Alcohol 75% v/v

Purpose

Antimicrobial

Use

Hand Sanitizer to decrease bacteria on the skin that could cause disease

Warnings

For external use only. Hands

Flammable. Keep away from heat and flame

When using this product, avoid contacting with face, eyes, and broken skin. In case of eye contacting, flush with plenty of water and seek medical advice.

Stop use and consult a doctor if irritation or redness occurs.

Keep out of reach of children. If swallowed, get medical help or contact a Poison Control Center right away.

Directions

Rub hands thoroughly with this product until dry

Children younger than 6 should be supervised by an adult when using

Other information

Do not store above 105F

May discolor some fabrics

Harmful to wood finishes and plastics

This product was not tested on animals

Inactive ingredients

Water